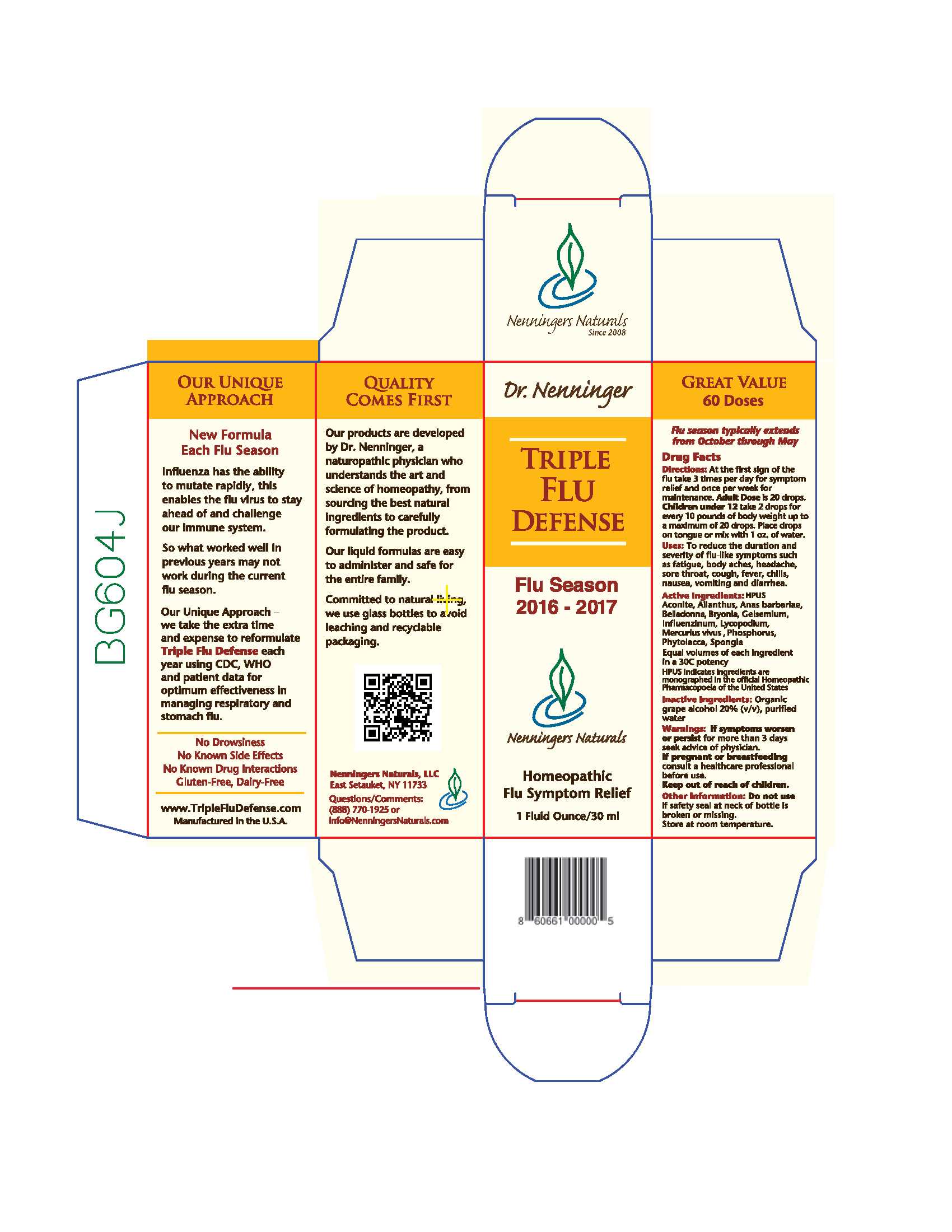 DRUG LABEL: Triple Flu Defense
NDC: 42731-022 | Form: LIQUID
Manufacturer: Nenningers Naturals, LLC
Category: homeopathic | Type: HUMAN OTC DRUG LABEL
Date: 20170207

ACTIVE INGREDIENTS: ACONITUM NAPELLUS ROOT 30 [hp_C]/30 mL; AILANTHUS ALTISSIMA FLOWERING TWIG 30 [hp_C]/30 mL; CAIRINA MOSCHATA HEART/LIVER AUTOLYSATE 30 [hp_C]/30 mL; ATROPA BELLADONNA 30 [hp_C]/30 mL; BRYONIA ALBA ROOT 30 [hp_C]/30 mL; GELSEMIUM SEMPERVIRENS ROOT 30 [hp_C]/30 mL; INFLUENZA A VIRUS A/CALIFORNIA/7/2009 (H1N1)-LIKE HEMAGGLUTININ ANTIGEN (PROPIOLACTONE INACTIVATED) 30 [hp_C]/30 mL; INFLUENZA B VIRUS B/PHUKET/3073/2013 HEMAGGLUTININ ANTIGEN (PROPIOLACTONE INACTIVATED) 30 [hp_C]/30 mL; INFLUENZA A VIRUS A/SWITZERLAND/9715293/2013 NIB-88 (H3N2) HEMAGGLUTININ ANTIGEN (PROPIOLACTONE INACTIVATED) 30 [hp_C]/30 mL; LYCOPODIUM CLAVATUM SPORE 30 [hp_C]/30 mL; MERCURY 30 [hp_C]/30 mL; PHOSPHORUS 30 [hp_C]/30 mL; PHYTOLACCA AMERICANA ROOT 30 [hp_C]/30 mL; SPONGIA OFFICINALIS SKELETON, ROASTED 30 [hp_C]/30 mL
INACTIVE INGREDIENTS: ALCOHOL; WATER

Dr. Nenninger Triple Flu Defense

Drug Facts

Directions: At first sign of the flu take 3 times per day for symptom relief and once per week for maintenance. Adult Dose is 20 drops. Children under 12 take 2 drops for every 10 pounds of body weight up to a maximum of 20 drops. Place drops on tongue or mix with 1 oz. of water.

PURPOSE

Homeopathic Flu Symptom Relief

INDICATIONS AND USAGE

Uses: To reduce the duration and severity of flu-like symptoms such as fatigue, body aches, headache, sore throat, cough, fever, chills, nausea, vomitting and diarrhea.

Active Ingredients: HPUS

Aconite, Ailanthus, Anas barbariae, Belladonna, Bryonia, Gelsemium, Influenzinum, Lycopodium, Mercurius vivus, Phosphorus, Phytolacca, Spongia

Equal volumes of each ingredient in a 30C potency.

HPUS indicates ingredients are monographed in th official Homeopathic Pharmacopeia of the United States

INACTIVE INGREDIENT

Inactive Ingredients: Organic grape alcohol 20% (v/v), purified water

Warnings

ASK DOCTOR

If symptoms worsen or persist for more than 3 days seek advice of physician.

PREGNANCY OR BREAST FEEDING

If pregnant or breastfeeding consult a healthcare professional before use.

Keep out of reach of children.

Other Information: Do not use if safety seal at neck of bottle is broken or missing.

Store at room temperature.

PACKAGE LABEL

Dr. Nenninger

Triple Flu Defense

Flu Season 2016 - 2017

Nenningers Naturals

Homeopathic Flu Symptom Relief

1 Fluid Ounce/30 ml